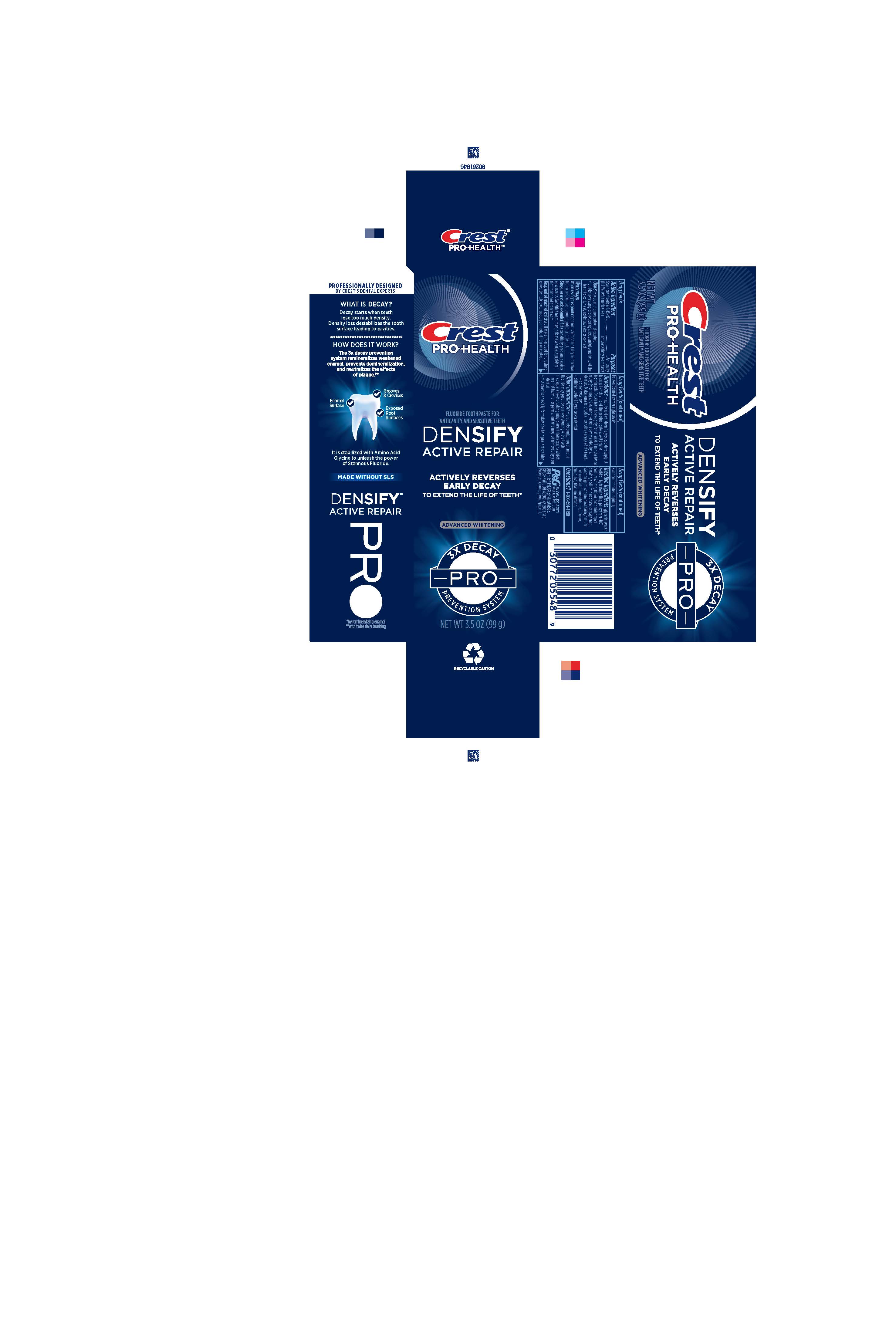 DRUG LABEL: Crest Pro-Health
NDC: 69423-754 | Form: PASTE, DENTIFRICE
Manufacturer: The Procter & Gamble Manufacturing Company
Category: otc | Type: HUMAN OTC DRUG LABEL
Date: 20260108

ACTIVE INGREDIENTS: STANNOUS FLUORIDE 1.5 mg/1 g
INACTIVE INGREDIENTS: POLOXAMER 407; GLYCINE; SODIUM HYDROXIDE; SACCHARIN SODIUM; TITANIUM DIOXIDE; COCAMIDOPROPYL BETAINE; SUCRALOSE; STANNOUS CHLORIDE; XANTHAN GUM; SODIUM CITRATE; WATER; HYDRATED SILICA; CARRAGEENAN; SODIUM GLUCONATE; GLYCERIN; SORBITOL

Crest Pro-Health Densify Pro Advanced Whitening

Drug Facts

Active ingredient

Stannous fluoride 0.454%

(0.15% w/v fluoride ion)

Purposes

Anticavity, antisensitivity toothpaste

Uses

- aids in the prevention of cavities
- builds increasing protection against painful sensitivity of the teeth to cold, heat, acids, sweets, or contact

WARNINGS

When using this product do not use for sensitivity longer than four weeks unless recommended by a dentist.

Stop use and ask a dentist if the sensitivity problem persists or worsens. Sensitive teeth may indicate a serious problem that may need prompt care.

Keep out of reach of children. If more than used for brushing is accidentally swallowed, get medical help or contact a Poison Control Center right away.

Directions

- adults and children 12 yrs. & older: apply at least a 1-inch strip of the product onto a soft bristle toothbrush. Brush teeth thoroughly for at least 1 minute twice a day (morning and evening) or as recommended by a dentist. Make sure to brush all sensitive areas of the teeth
- do not swallow
- children under 12 yrs. of age: ask a dentist

Other information

- products containing stannous fluoride may produce surface staining of the teeth
- adequate toothbrushing may prevent these stains which are not harmful or permanent and may be removed by your dentist
- this Crest is specially formulated to help prevent staining
- see your dentist regularly

Inactive ingredients

glycerin, sorbitol, water, hydrated silica, sodium lauryl sulfate, sodium citrate, flavor, sodium gluconate, carrageenan, xanthan gum, sodium saccharin, cocamidopropyl betaine, sodium hydroxide, stannous chloride, sucralose, titanium dioxide

Questions?

1-800-594-4158

DISTR. BY PROCTER & GAMBLE,

CINCINNATI, OH 45202

Principal Display Panel - 99 g tube in carton

Crest

PRO HEALTH

FLUORIDE TOOTHPASTE FOR ANTICAVITY AND SENSITIVE TEETH

DENSIFY

ACTIVE REPAIR

ACTIVELY REVERSES

EARLY DECAY

TO EXTEND THE LIFE OF TEETH*

ADVANCED WHITENING

3X DECAY

PRO

PREVENTION SYSTEM

NET WT 3.5 OZ (99g)